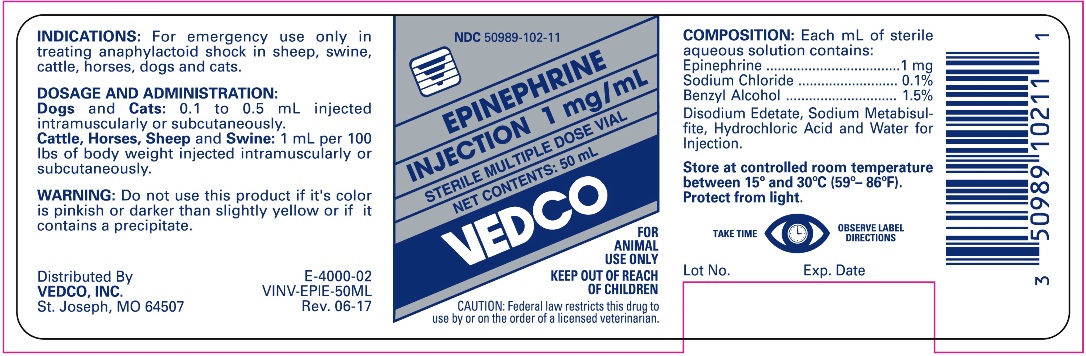 DRUG LABEL: EPINEPHRINE
NDC: 50989-102 | Form: INJECTION
Manufacturer: Vedco, Inc.
Category: animal | Type: PRESCRIPTION ANIMAL DRUG LABEL
Date: 20250304

ACTIVE INGREDIENTS: EPINEPHRINE 1 mg/1 mL
INACTIVE INGREDIENTS: EDETATE DISODIUM

EPINEPHRINE INJECTION 1 mg/mL STERILE MULTIPLE DOSE VIAL

INDICATIONS AND USAGE

FOR ANIMAL USE ONLY

KEEP OUT OF REACH OF CHILDREN

CAUTION: Federal law restricts this drug to use by or on the order of a licensed veterinarian.

INDICATIONS

For emergency use only in treating anaphylactoid shock in sheep, swine, cattle, horses, dogs and cats.

DOSAGE AND ADMINISTRATION

Dogs and Cats: 0.1 to 0.5 mL injected Intramuscularly or Subcutaneously.
Cattle, Horses, Sheep and Swine: 1 mL per 100 lbs of body weight injected intramuscularly or subcutaneously.

WARNING

Do not use this product if it's color is pinkish or darker than slightly yellow or if it contains a precipitate.

COMPOSITION

Each mL of sterile aqueous solution contains:
Epinephrine ....................... 1 mg
Sodium Chloride ................ 0.1%
Benzyl Alcohol .................. 1.5%
Disodium Edetate, Sodium Metabisulfite, Hydrochloric Acid, and Water for Injection.

STORAGE AND HANDLING

Store at controlled room temperature between 15° and 30°C (59°-86°F).

Protect from light.

TAKE TIME OBSERVE LABEL DIRECTIONS